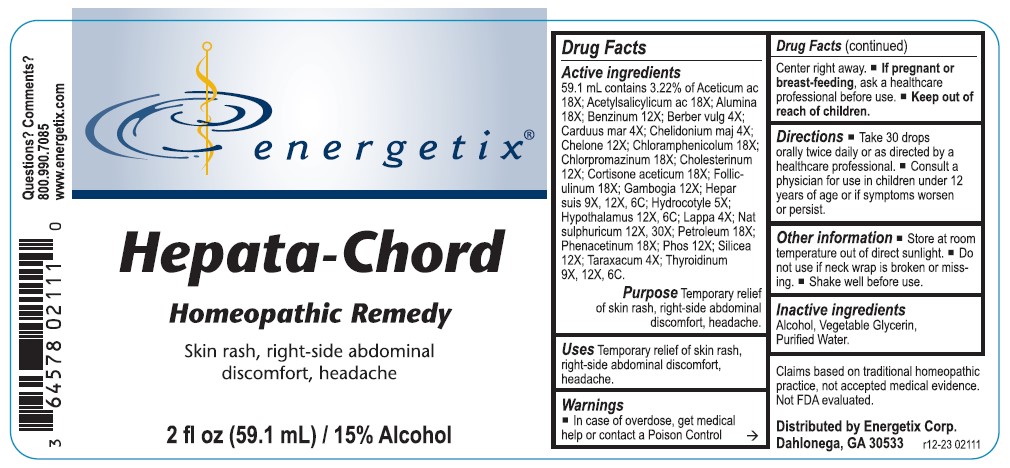 DRUG LABEL: Hepata-Chord
NDC: 64578-0176 | Form: LIQUID
Manufacturer: Energetix Corporation
Category: homeopathic | Type: HUMAN OTC DRUG LABEL
Date: 20241217

ACTIVE INGREDIENTS: ACETIC ACID 18 [hp_X]/59.1 mL; ASPIRIN 18 [hp_X]/59.1 mL; ALUMINUM OXIDE 18 [hp_X]/59.1 mL; BENZENE 12 [hp_X]/59.1 mL; BERBERIS VULGARIS ROOT BARK 4 [hp_X]/59.1 mL; MILK THISTLE 4 [hp_X]/59.1 mL; CHELIDONIUM MAJUS 4 [hp_X]/59.1 mL; CHELONE GLABRA 12 [hp_X]/59.1 mL; CHLORAMPHENICOL 18 [hp_X]/59.1 mL; CHLORPROMAZINE 18 [hp_X]/59.1 mL; CHOLESTEROL 12 [hp_X]/59.1 mL; CORTISONE ACETATE 18 [hp_X]/59.1 mL; ESTRONE 18 [hp_X]/59.1 mL; GAMBOGE 12 [hp_X]/59.1 mL; PORK LIVER 9 [hp_X]/59.1 mL; CENTELLA ASIATICA 5 [hp_X]/59.1 mL; BOS TAURUS HYPOTHALAMUS
 12 [hp_X]/59.1 mL; ARCTIUM LAPPA ROOT 4 [hp_X]/59.1 mL; SODIUM SULFATE 12 [hp_X]/59.1 mL; KEROSENE 18 [hp_X]/59.1 mL; PHENACETIN 18 [hp_X]/59.1 mL; PHOSPHORUS 12 [hp_X]/59.1 mL; SILICON DIOXIDE 12 [hp_X]/59.1 mL; TARAXACUM OFFICINALE 4 [hp_X]/59.1 mL; THYROID, UNSPECIFIED 9 [hp_X]/59.1 mL
INACTIVE INGREDIENTS: WATER; GLYCERIN; ALCOHOL

Hepata-Chord

ACTIVE INGREDIENT

Active ingredients59.1 mL contains 3.22% of: Aceticum ac 18X; Acetylsalicylicum ac 18X; Alumina 18X; Benzinum 12X; Berberis vulg 4X; Carduus mar 4X; Chelidonium maj 4X; Chelone 12X; Chloramphenicolum 18X; Chlorpromazinum 18X; Cholesterinum 12X; Cortisone aceticum 18X; Folliculinum 18X; Gambogia 12X; Hepar suis 9X, 12X, 6C; Hydrocotyle 5X; Hypothalamus 12X, 6C; Lappa 4X; Nat sulphuricum 12X, 30X; Petroleum 18X; Phenacetinum 18X; Phos 12X; Silicea 12X; Taraxacum 4X; Thyroidinum 9X, 12X, 6C.

Claims based on traditional homeopathic practice, not accepted medical evidence. Not FDA evaluated.

Uses

Temporary relief of skin rash, right-side abdominal discomfort, headache

Warnings

- In case of overdose, get medical help or contact a Poison Control Center right away.
- If pregnant or breast feeding, ask a health professional before use.

• Keep out of reach of children.

Directions

- Take 30 drops orally twice daily or as directed by a healthcare professional.
- Consult a physician for use in children under 12 years of age or if symptoms worsen or persist.

Other information

- Store at room temperature out of direct sunlight.
- Do not use if neck wrap is broken or missing.
- Shake well before use.

Inactive ingredients

Alcohol, Vegetable Glycerin, Purified Water.

QUESTIONS

Distributed by Energetix Corp.

Dahlonega, GA 30533

Questions? Comments?

800.990.7085

www.energetix.com

PACKAGE LABEL

energetix®

Hepata-Chord

Homeopathic Remedy

Skin rash, right-side abdominal discomfort, headache

2 fl oz (59.1 mL) / 15% Alcohol

PURPOSE

Purpose Temporary relief on skin rash, right-side abdominal discomfort, headache